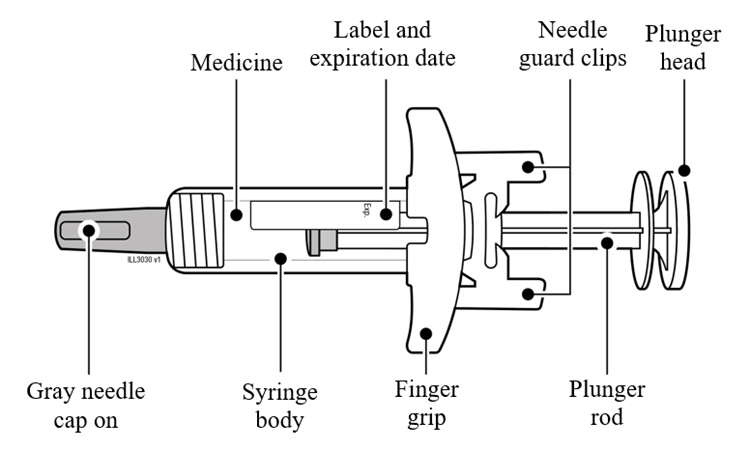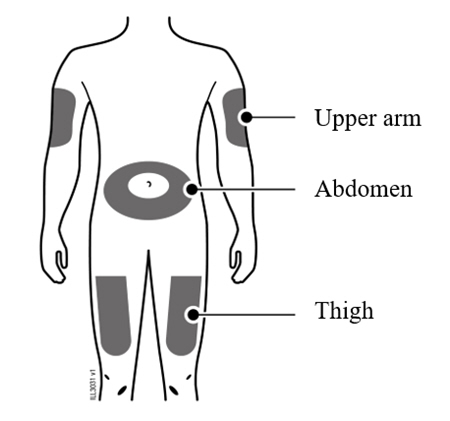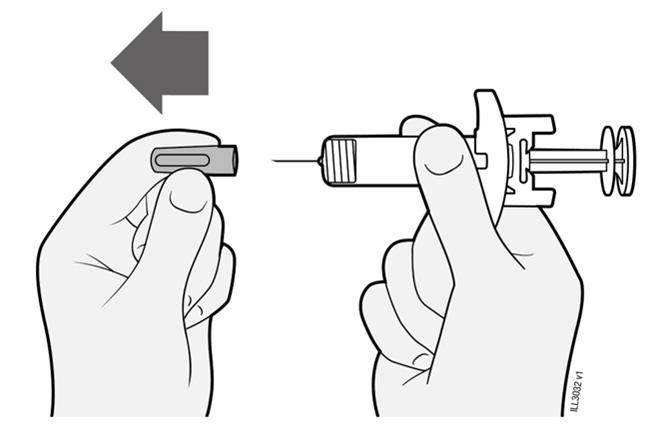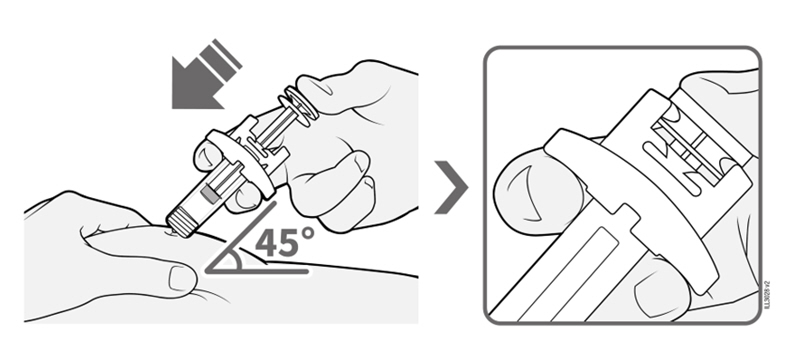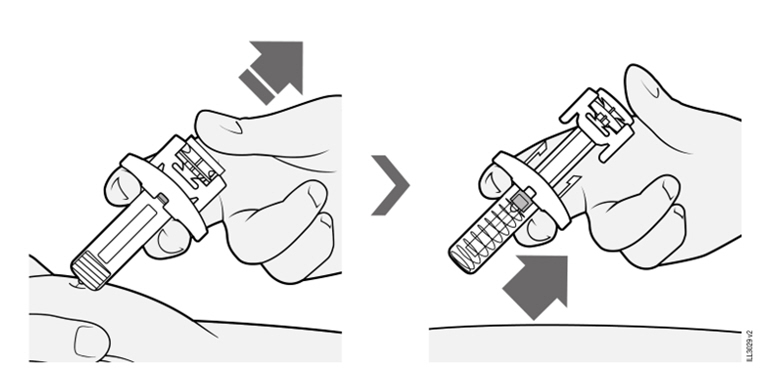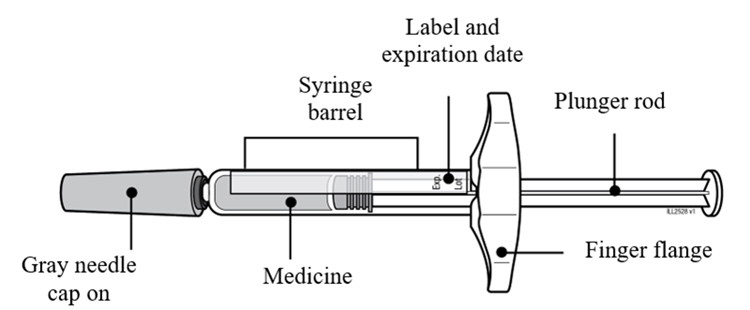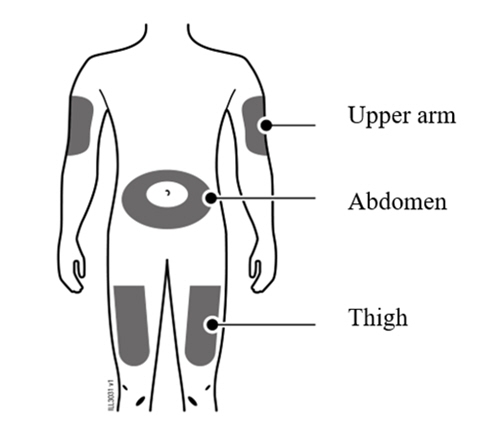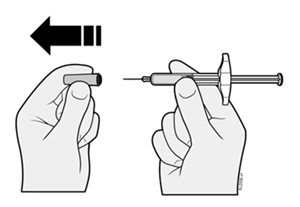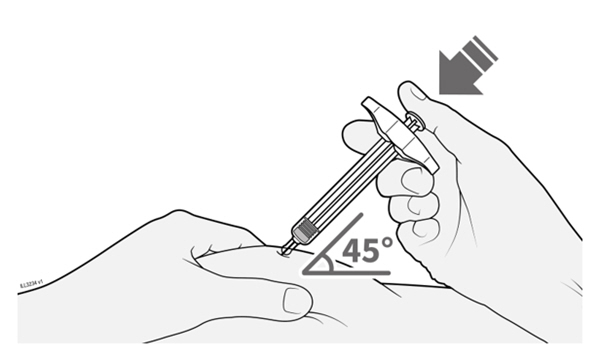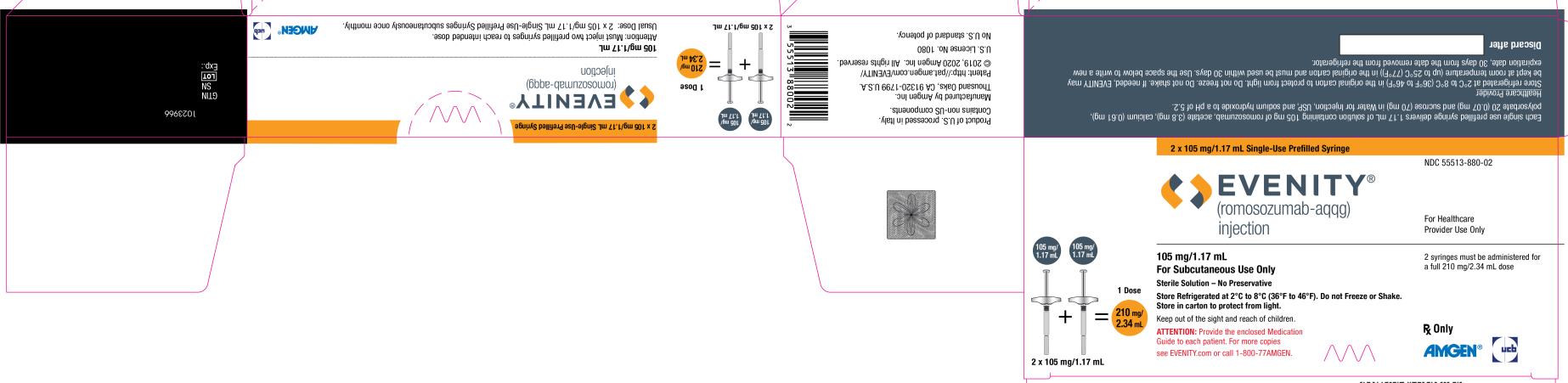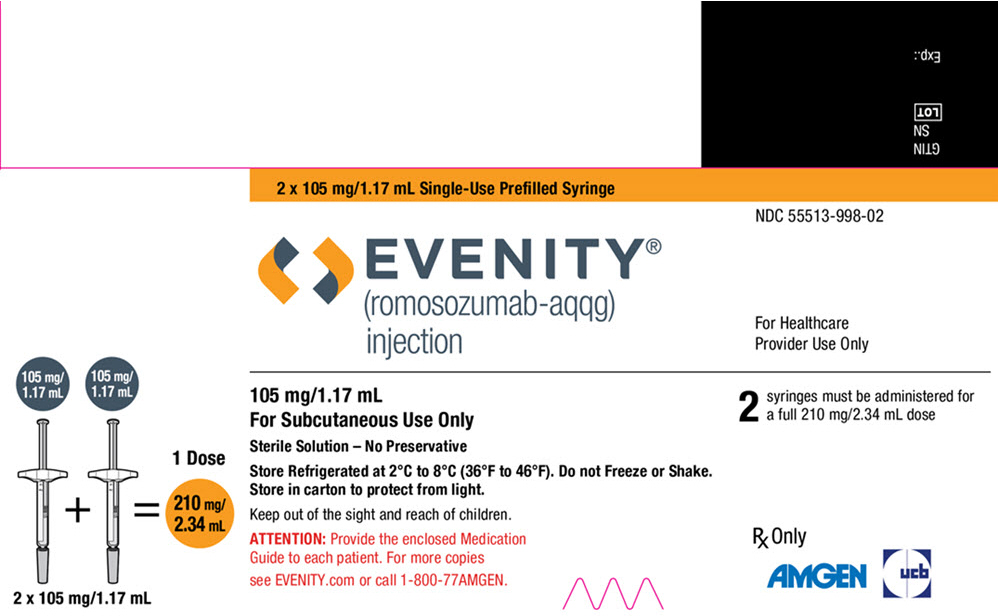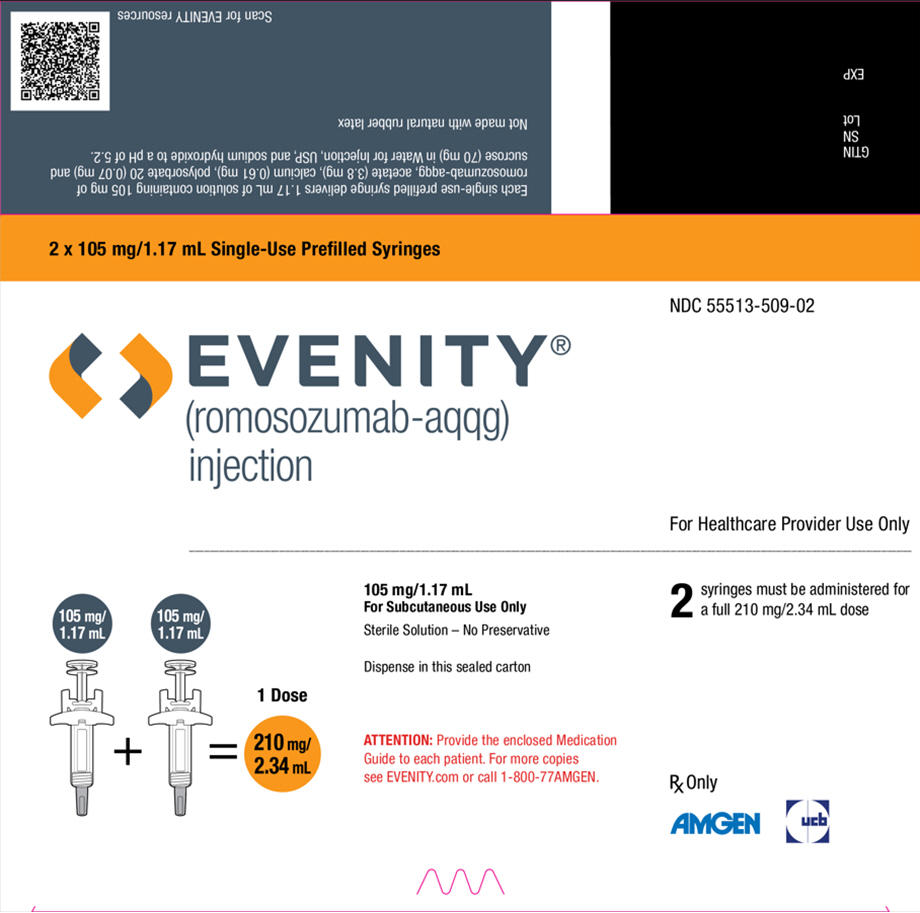 DRUG LABEL: Evenity
NDC: 55513-880 | Form: INJECTION, SOLUTION
Manufacturer: Amgen, Inc
Category: prescription | Type: HUMAN PRESCRIPTION DRUG LABEL
Date: 20260108

ACTIVE INGREDIENTS: ROMOSOZUMAB 105 mg/1.17 mL
INACTIVE INGREDIENTS: ACETATE ION 3.8 mg/1.17 mL; CALCIUM 0.61 mg/1.17 mL; POLYSORBATE 20 0.07 mg/1.17 mL; SUCROSE 70 mg/1.17 mL; SODIUM HYDROXIDE; WATER

HIGHLIGHTS OF PRESCRIBING INFORMATION

These highlights do not include all the information needed to use EVENITY safely and effectively. See full prescribing information for EVENITY.
EVENITY® (romosozumab-aqqg) injection, for subcutaneous use
Initial U.S. Approval: 2019

WARNING: POTENTIAL RISK OF MYOCARDIAL INFARCTION, STROKE AND CARDIOVASCULAR DEATH

See full prescribing information for complete boxed warning.

- EVENITY may increase the risk of myocardial infarction, stroke and cardiovascular death. (5.1)
- EVENITY should not be initiated in patients who have had a myocardial infarction or stroke within the preceding year. Consider whether the benefits outweigh the risks in patients with other cardiovascular risk factors. (5.1)
- If a patient experiences a myocardial infarction or stroke during therapy, EVENITY should be discontinued. (5.1)

RECENT MAJOR CHANGES

Dosage and Administration (2.3) | 1/2026

1 INDICATIONS AND USAGE

EVENITY is a sclerostin inhibitor indicated for the treatment of osteoporosis in postmenopausal women at high risk for fracture, defined as a history of osteoporotic fracture, or multiple risk factors for fracture; or patients who have failed or are intolerant to other available osteoporosis therapy. (1)

Limitations of Use: Limit duration of use to 12 monthly doses. If osteoporosis therapy remains warranted, continued therapy with an anti-resorptive agent should be considered. (1.2)

2 DOSAGE AND ADMINISTRATION

- Two separate subcutaneous injections are needed to administer the total dose of 210 mg. Inject two syringes, one after the other. (2.1)
- Should be administered by a healthcare provider. (2.1)
- Administer 210 mg subcutaneously once every month for 12 doses in the abdomen, thigh, or upper arm. (2.2)
- Adequately supplement calcium and vitamin D during treatment. (2.2)

3 DOSAGE FORMS AND STRENGTHS

Injection: 105 mg/1.17 mL solution in a single-use prefilled syringe. A full dose of EVENITY requires two single-use prefilled syringes. (3)

4 CONTRAINDICATIONS

- Hypocalcemia (4)
- Known hypersensitivity to EVENITY (4)

5 WARNINGS AND PRECAUTIONS

- Major Adverse Cardiac Events (MACE): Monitor for symptoms of MI and stroke and seek prompt medical attention if symptoms occur. (5.1)
- Hypersensitivity: Hypersensitivity reactions, including angioedema, erythema multiforme, dermatitis, rash, and urticaria. Discontinue EVENITY if a clinically significant allergic reaction occurs. (5.2)
- Hypocalcemia: Adequately supplement calcium and vitamin D during treatment with EVENITY. (5.3)
- Osteonecrosis of the Jaw: Monitor for symptoms. Consider discontinuation of therapy based on benefit-risk assessment. (5.4)
- Atypical Femoral Fracture: Evaluate new or unusual thigh, hip, or groin pain to rule out an incomplete femur fracture. (5.5)

6 ADVERSE REACTIONS

The most common adverse reactions (≥ 5%) reported with EVENITY in clinical trials were arthralgia and headache. (6.1)

To report SUSPECTED ADVERSE REACTIONS, contact Amgen Inc. at 1-800-77-AMGEN (1-800-772-6436) or FDA at 1-800-FDA-1088 or www.fda.gov/medwatch.

8 USE IN SPECIFIC POPULATIONS

Renal Impairment: Patients with severe renal impairment or receiving dialysis are at greater risk of developing hypocalcemia. Monitor serum calcium and supplement with calcium and vitamin D. (5.3, 8.7)

FULL PRESCRIBING INFORMATION

WARNING: POTENTIAL RISK OF MYOCARDIAL INFARCTION, STROKE AND CARDIOVASCULAR DEATH

- EVENITY may increase the risk of myocardial infarction, stroke, and cardiovascular death [see Warnings and Precautions (5.1)]. EVENITY should not be initiated in patients who have had a myocardial infarction or stroke within the preceding year. Consider whether the benefits outweigh the risks in patients with other cardiovascular risk factors. If a patient experiences a myocardial infarction or stroke during therapy, EVENITY should be discontinued.

1 INDICATIONS AND USAGE

1.1 Treatment of Postmenopausal Women with Osteoporosis at High Risk for Fracture

EVENITY is indicated for the treatment of osteoporosis in postmenopausal women at high risk for fracture, defined as a history of osteoporotic fracture, or multiple risk factors for fracture; or patients who have failed or are intolerant to other available osteoporosis therapy.

1.2 Limitations of Use

The anabolic effect of EVENITY wanes after 12 monthly doses of therapy. Therefore, the duration of EVENITY use should be limited to 12 monthly doses. If osteoporosis therapy remains warranted, continued therapy with an anti-resorptive agent should be considered [see Dosage and Administration (2.2) and Clinical Studies (14.1)].

2 DOSAGE AND ADMINISTRATION

2.1 Important Dosage and Administration Instructions

- Two separate syringes (and two separate subcutaneous injections) are needed to administer the total dose of 210 mg of EVENITY. Inject two 105 mg/1.17 mL prefilled syringes, one after the other.
- EVENITY should be administered by a healthcare provider.

2.2 Recommended Dosage

- The recommended dose of EVENITY is 210 mg administered subcutaneously in the abdomen, thigh or upper arm. Administer EVENITY once every month.
- The treatment duration for EVENITY is 12 monthly doses.
- Patients should be adequately supplemented with calcium and vitamin D during treatment with EVENITY [see Warnings and Precautions (5.3) and Clinical Studies (14.1)].
- If the EVENITY dose is missed, administer as soon as it can be rescheduled. Thereafter, EVENITY can be scheduled every month from the date of the last dose.

2.3 Preparation and Administration Instructions

Administration instructions: Prefilled syringe with automatic needle guard:

Step 1: Prior to Administration:

- Remove two syringes from the carton.
- Visually inspect EVENITY for particles and discoloration prior to administration. EVENITY is a clear to opalescent, colorless to light yellow solution. Do not use if the solution is cloudy or discolored or contains particles.
- Do not use the syringe if
  - any part appears cracked or broken
  - the gray needle cap is missing or not securely attached
  - the expiration date printed on the label has passed
  - the syringe has been dropped on a hard surface
- Always hold the syringe by the syringe body to remove the syringe from the tray. See Figure A.
  - Do not grasp the plunger rod.
  - Do not grasp the gray needle cap.
  - Do not remove the gray needle cap until you are ready to inject.
- Allow EVENITY to sit at room temperature for at least 30 minutes before injecting. Do not warm in any other way [see How Supplied/Storage and Handling (16)].

Figure A

Step 2: Select the Injection Site and Prepare the Syringe

Prepare and clean two injection sites, one for each of the two injections. See Figure B.

Figure B

The recommended subcutaneous injection sites include:

- The thigh
- Abdomen, except for a two-inch area right around the navel
- Outer area of upper arm

Clean the injection sites with alcohol wipes. Let the skin dry.

- Choose a different site each time you give an injection. If you want to use the same injection site, make sure it is not the same spot on the injection site you used for a previous injection.
- Do not inject into areas where the skin is tender, bruised, red, or hard. Avoid injecting into areas with scars or stretch marks.

Choose the first syringe. Pull the gray needle cap straight off and away from your body when you are ready to inject. See Figure C.

Figure C

- Do not put the gray needle cap back onto the syringe.
- Do not leave the cap off for more than 5 minutes as this can dry out the solution.
- The prefilled syringe may contain air bubbles. Do not try to push air bubbles out as it is normal to see air bubbles.

Step 3: Inject EVENITY

Pinch the skin around the injection site before injecting. Insert the needle into the pinched skin at or about a 45-degree angle. Slowly press the plunger head all the way down with your thumb until it is completely between the needle guard clips. Do not pull back on the plunger rod at any time. Do not remove the syringe until all the medicine has been injected. Do not administer into muscle or blood vessel. See Figure D.

Figure D

Slowly release pressure on the plunger head with your thumb and remove the syringe from the skin. Let go of the skin after the needle is removed. Releasing the plunger head covers the used needle. See Figure E.

Figure E

Step 4: Syringe and Gray Needle Cap Disposal

Immediately dispose of the syringe and needle cap in the nearest sharps container.

Important: Repeat all steps with the second syringe to inject the full dose.

Administration instructions: Prefilled syringe:

Step 1: Prior to Administration:

- Remove two syringes from the carton.
- Visually inspect EVENITY for particles and discoloration prior to administration. EVENITY is a clear to opalescent, colorless to light yellow solution. Do not use if the solution is cloudy or discolored or contains particles.
- Do not use the syringe if
  - any part appears cracked or broken
  - the gray needle cap is missing or not securely attached
  - the expiration date printed on the label has passed
  - the syringe has been dropped on a hard surface
- Always hold the prefilled syringe by the syringe barrel to remove the syringe from the tray. See Figure F.
  - Do not grasp the plunger rod.
  - Do not grasp the gray needle cap.
  - Do not remove the gray needle cap until you are ready to inject.
- Allow EVENITY to sit at room temperature for at least 30 minutes before injecting. Do not warm in any other way [see How Supplied/Storage and Handling (16)].

Figure F

Step 2: Select the Injection Site and Prepare the Syringe

Prepare and clean two injection sites, one for each of the two injections. See Figure G.

Figure G

The recommended subcutaneous injection sites include:

- The thigh
- Abdomen, except for a two-inch area right around the navel
- Outer area of upper arm

Clean the injection sites with alcohol wipes. Let the skin dry.

- Choose a different site each time you give an injection. If you want to use the same injection site, make sure it is not the same spot on the injection site you used for a previous injection.
- Do not inject into areas where the skin is tender, bruised, red, or hard. Avoid injecting into areas with scars or stretch marks.

Choose the first syringe. Pull the gray needle cap straight off and away from your body when you are ready to inject. See Figure H.

Figure H

- Do not put the gray needle cap back onto the syringe.
- Do not leave the cap off for more than 5 minutes as this can dry out the solution.
- The prefilled syringe may contain air bubbles. Do not try to push air bubbles out as it is normal to see air bubbles.

Step 3: Inject EVENITY

Pinch the skin around the injection site before injecting. Insert the needle into the pinched skin at or about a 45-degree angle. Insert needle and inject all the liquid subcutaneously. Do not administer into muscle or blood vessel. See Figure I.

Figure I

When done, gently lift the syringe off of the skin.

Step 4: Syringe and Needle Cap Disposal

Immediately dispose of the syringe and needle cap in the nearest sharps container.

Important: Repeat all steps with the second syringe to inject the full dose.

3 DOSAGE FORMS AND STRENGTHS

- Injection: 105 mg/1.17 mL clear to opalescent, colorless to light yellow solution in a single-use prefilled syringe.

A full dose of EVENITY requires two single-use prefilled syringes.

4 CONTRAINDICATIONS

EVENITY is contraindicated in patients with:

- Hypocalcemia. Pre-existing hypocalcemia must be corrected prior to initiating therapy with EVENITY [see Warnings and Precautions (5.3), Adverse Reactions (6.1) and Use in Specific Populations (8.7)].
- A history of systemic hypersensitivity to romosozumab-aqqg or to any component of the product formulation. Reactions have included angioedema, erythema multiforme, and urticaria [see Warnings and Precautions (5.2) and Adverse Reactions (6.1)].

5 WARNINGS AND PRECAUTIONS

5.1 Major Adverse Cardiac Events (MACE)

In a randomized controlled trial in postmenopausal women, there was a higher rate of major adverse cardiac events (MACE), a composite endpoint of cardiovascular death, nonfatal myocardial infarction and nonfatal stroke, in patients treated with EVENITY compared to those treated with alendronate [see Boxed Warning and Adverse Reactions (6.1)].

EVENITY should not be initiated in patients who have had a myocardial infarction or stroke within the preceding year. Consider whether the benefits outweigh the risks in patients with other cardiovascular risk factors. Monitor for signs and symptoms of myocardial infarction and stroke and instruct patients to seek prompt medical attention if symptoms occur. If a patient experiences a myocardial infarction or stroke during therapy, EVENITY should be discontinued.

5.2 Hypersensitivity Reactions

Hypersensitivity reactions, including angioedema, erythema multiforme, dermatitis, rash, and urticaria have occurred in EVENITY-treated patients. If an anaphylactic or other clinically significant allergic reaction occurs, initiate appropriate therapy and discontinue further use of EVENITY [see Contraindications (4) and Adverse Reactions (6.1)].

5.3 Hypocalcemia

Hypocalcemia has occurred in patients receiving EVENITY. Correct hypocalcemia prior to initiating EVENITY [see Contraindications (4), Adverse Reactions (6.1) and Use in Specific Populations (8.7)]. Monitor patients for signs and symptoms of hypocalcemia. Patients should be adequately supplemented with calcium and vitamin D while on EVENITY [see Dosage and Administration (2.2) and Clinical Studies (14.1)].

Patients with severe renal impairment (estimated glomerular filtration rate [eGFR] 15 to 29 mL/min/1.73 m^2) or receiving dialysis are at greater risk of developing hypocalcemia. Monitor serum calcium and adequately supplement patients who have severe renal impairment or are receiving dialysis with calcium and vitamin D. Instruct patients with severe renal impairment, including those receiving dialysis, about the symptoms of hypocalcemia and the importance of maintaining calcium levels with adequate calcium and vitamin D supplementation.

5.4 Osteonecrosis of the Jaw

Osteonecrosis of the jaw (ONJ), which can occur spontaneously, is generally associated with tooth extraction and/or local infection with delayed healing, and has been reported in patients receiving EVENITY. A routine oral examination should be performed by the prescriber prior to initiation of EVENITY treatment. Concomitant administration of drugs associated with ONJ (chemotherapy, bisphosphonates, denosumab, angiogenesis inhibitors, and corticosteroids) may increase the risk of developing ONJ. Other risk factors for ONJ include cancer, radiotherapy, poor oral hygiene, pre-existing dental disease or infection, anemia, and coagulopathy [see Adverse Reactions (6.1)].

For patients requiring invasive dental procedures, clinical judgment of the treating physician and/or oral surgeon should guide the management plan of each patient based on benefit-risk assessment. Patients who are suspected of having or who develop ONJ while on EVENITY should receive care by a dentist or an oral surgeon. In these patients, dental surgery to treat ONJ may exacerbate the condition. Discontinuation of EVENITY should be considered based on benefit-risk assessment.

5.5 Atypical Subtrochanteric and Diaphyseal Femoral Fractures

Atypical low-energy or low trauma fractures of the femoral shaft have been reported in patients receiving EVENITY [see Adverse Reactions (6.1)]. These fractures can occur anywhere in the femoral shaft from just below the lesser trochanter to above the supracondylar flare and are transverse or short oblique in orientation without evidence of comminution. Causality has not been established as these fractures also occur in osteoporotic patients who have not been treated.

Atypical femoral fractures most commonly occur with minimal or no trauma to the affected area. They may be bilateral and many patients report prodromal pain in the affected area, usually presenting as dull, aching thigh pain, weeks to months before a complete fracture occurs.

During EVENITY treatment, patients should be advised to report new or unusual thigh, hip, or groin pain. Any patient who presents with thigh or groin pain should be suspected of having an atypical fracture and should be evaluated to rule out an incomplete femur fracture. Patient presenting with an atypical femur fracture should also be assessed for symptoms and signs of fracture in the contralateral limb. Interruption of EVENITY therapy should be considered based on benefit-risk assessment [see Clinical Studies (14)].

6 ADVERSE REACTIONS

The following adverse reactions are discussed in greater detail in other sections of the label:

- Major adverse cardiac events [see Boxed Warning and Warnings and Precautions (5.1)]
- Hypersensitivity [see Contraindications (4) and Warnings and Precautions (5.2)]
- Hypocalcemia [see Contraindications (4) and Warnings and Precautions (5.3)]
- Osteonecrosis of the Jaw [see Warnings and Precautions (5.4)]
- Atypical Subtrochanteric and Diaphyseal Femoral Fractures [see Warnings and Precautions (5.5)]

6.1 Clinical Trials Experience

Because clinical trials are conducted under widely varying conditions, adverse reaction rates observed in the clinical trials of a drug cannot be directly compared to rates in the clinical trials of another drug and may not reflect the rates observed in practice.

The safety of EVENITY for the treatment of postmenopausal osteoporosis was evaluated in a multicenter, randomized, double-blind, placebo-controlled study (Study 1, NCT01575834) of 7180 postmenopausal women aged 55 to 90 years (mean age of 71 years). A total of 3581 and 3576 women received at least one dose of EVENITY and placebo, respectively, administered once every month during the 12-month double-blind study period. Women received at least 500 mg calcium and 600 international units of vitamin D supplementation daily and 77% received a loading dose of 50,000 to 60,000 international units of vitamin D within one week of randomization (if serum 25-hydroxyvitamin D concentrations were 40 ng/mL or less).

The safety of EVENITY for the treatment of postmenopausal osteoporosis in patients at high risk of fracture was evaluated in a multicenter, randomized, double-blind, alendronate-controlled study (Study 2, NCT01631214) of 4093 postmenopausal women aged 55 to 90 years (mean age of 74 years). A total of 2040 and 2014 women received at least one dose of EVENITY and alendronate, respectively, during the 12-month double-blind study period. Women received at least 500 mg calcium and 600 international units vitamin D supplementation daily and 74% received a loading dose of 50,000 to 60,000 international units of vitamin D within one week of randomization (if serum 25-hydroxyvitamin D concentrations were 40 ng/mL or less).

In Study 1, during the 12-month double-blind treatment period, the incidence of all-cause mortality was 0.7% (24/3576) in the placebo group and 0.8% (29/3581) in the EVENITY group. The incidence of nonfatal serious adverse events was 8.3% in the placebo group and 9.1% in the EVENITY group. The percentage of patients who withdrew from the study due to adverse events was 1.1% in the placebo group and 1.1% in the EVENITY group. The most common adverse reactions reported with EVENITY (greater than or equal to 5% and at a higher incidence than placebo) were arthralgia and headache. The most common adverse reaction leading to discontinuation of EVENITY was arthralgia (6 subjects [0.2%] in the placebo group and 5 subjects [0.1%] in the EVENITY group).

In Study 2, during the 12-month double-blind treatment period, the incidence of all-cause mortality was 1.1% (22/2014) in the alendronate group and 1.5% (30/2040) in the EVENITY group. The incidence of nonfatal serious adverse events was 13.3% in the alendronate group and 11.9% in the EVENITY group. The percentage of patients who withdrew from the study due to adverse events was 1.2% in the alendronate group and 1.2% in the EVENITY group. The most common adverse reactions reported with EVENITY (greater than or equal to 5%) were arthralgia and headache.

Table 1 outlines the most common adverse reactions occurring in greater than or equal to 2% of EVENITY-treated women in at least one study.

Table 1. Adverse Reactions Occurring in ≥ 2% of EVENITY-Treated Women in at Least One Study (Studies 1 and 2)
 | Study 1 |  | Study 2
Preferred Term | Placebo (N = 3576) n (%) | EVENITY (N = 3581) n (%) | Alendronate (N = 2014) n (%) | EVENITY (N = 2040) n (%)
Arthralgia | 434 (12.1) | 468 (13.1) | 194 (9.6) | 166 (8.1)
Headache | 208 (5.8) | 235 (6.6) | 110 (5.5) | 106 (5.2)
Muscle spasms | 140 (3.9) | 163 (4.6) | 81 (4.0) | 70 (3.4)
Edema peripheral | 67 (1.9) | 86 (2.4) | 38 (1.9) | 34 (1.7)
Asthenia | 79 (2.2) | 84 (2.3) | 53 (2.6) | 50 (2.5)
Neck pain | 54 (1.5) | 80 (2.2) | 42 (2.1) | 34 (1.7)
Insomnia | 68 (1.9) | 72 (2.0) | 36 (1.8) | 34 (1.7)
Paresthesia | 62 (1.7) | 72 (2.0) | 34 (1.7) | 29 (1.4)

The adverse reactions described below are from the 12-month treatment periods of Study 1 (placebo-controlled) and Study 2 (alendronate-controlled).

Major Adverse Cardiac Events (MACE)

During the 12-month double-blind treatment period of the placebo-controlled trial (Study 1), myocardial infarction occurred in 9 (0.3%) women in the EVENITY group and 8 (0.2%) women in the placebo group; stroke occurred in 8 (0.2%) women in the EVENITY group and 10 (0.3%) women in the placebo group. These events occurred in patients with and without a history of myocardial infarction or stroke.

Cardiovascular death occurred in 17 (0.5%) women in the EVENITY group and 15 (0.4%) women in the placebo group. The number of women with positively adjudicated MACE was 30 (0.8%) in the EVENITY group and 29 (0.8%) in the placebo group, yielding a hazard ratio of 1.03 (95% confidence interval [0.62, 1.72]) for EVENITY compared to placebo.

During the 12-month double-blind treatment period of the active-controlled trial (Study 2), myocardial infarction occurred in 16 (0.8%) women in the EVENITY group and 5 (0.2%) women in the alendronate group; stroke occurred in 13 (0.6%) women in the EVENITY group and 7 (0.3%) women in the alendronate group. These events occurred in patients with and without a history of myocardial infarction or stroke. Cardiovascular death occurred in 17 (0.8%) women in the EVENITY group and 12 (0.6%) women in the alendronate group. The number of women with positively adjudicated MACE was 41 (2.0%) in the EVENITY group and 22 (1.1%) in the alendronate group, yielding a hazard ratio of 1.87 (95% confidence interval [1.11, 3.14]) for EVENITY compared to alendronate [see Boxed Warning and Warnings and Precautions (5.1)].

Hypersensitivity Reactions

Across both trials, hypersensitivity reactions were reported in 364 (6.5%) women in the EVENITY group and 365 (6.5%) women in the control group. Reported reactions included angioedema (3 [< 0.1%] women in the EVENITY group vs. 3 [< 0.1%] women in the control group), erythema multiforme (1 [< 0.1%] woman in the EVENITY group vs. no woman in the control group), dermatitis (32 [0.6%] women in the EVENITY group vs. 42 [0.8%] women in the control group), rash (60 [1.1%] women in the EVENITY group vs. 53 [0.9%] women in the control group), and urticaria (23 [0.4%] women in the EVENITY group vs. 27 [0.5%] women in the control group). Although angioedema, dermatitis and urticaria were not reported at a higher incidence with EVENITY than control, there were cases of angioedema, dermatitis and urticaria that were determined to be related to EVENITY use [see Contraindications (4) and Warnings and Precautions (5.2)].

Hypocalcemia

Across both trials, adverse events of hypocalcemia occurred in 2 EVENITY-treated women and in 1 woman in the control group. Decreases in albumin-adjusted serum calcium to below the lower limit of the reference range (8.3 mg/dL) were reported in 14 (0.2%) women in the EVENITY group and 10 (0.2%) women in the control group. No patient receiving EVENITY developed serum calcium less than 7.5 mg/dL. The nadir in albumin-adjusted serum calcium occurred by month 1 after EVENITY dosing in patients with normal renal function [see Contraindications (4) and Warnings and Precautions (5.3)].

Injection Site Reactions

Across both trials, injection site reactions occurred in 278 (4.9%) women in the EVENITY group and 157 (2.8%) women in the control group. The most common injection site reactions were pain (94 [1.7%] women in the EVENITY group; 70 [1.3%] women in the control group) and erythema (80 [1.4%] women in the EVENITY group and 14 [0.3%] women in the control group). Injection site reactions resulted in discontinuation of treatment in 7 (0.1%) EVENITY-treated patients and 3 (< 0.1%) patients in the control group.

Osteonecrosis of the Jaw

Across both trials, osteonecrosis of the jaw occurred in one patient during treatment with EVENITY [see Warnings and Precautions (5.4)].

Atypical Subtrochanteric and Diaphyseal Fractures

Across both trials, atypical femoral fracture occurred in one patient during treatment with EVENITY [see Warnings and Precautions (5.5)].

8 USE IN SPECIFIC POPULATIONS

8.1 Pregnancy

Risk Summary

EVENITY is not indicated for use in women of reproductive potential. In animal reproduction studies, weekly administration of romosozumab-aqqg to pregnant rats during the period of organogenesis at exposures greater than 31 times the clinical exposure produced skeletal abnormalities in the offspring. Administration of romosozumab-aqqg to rats prior to mating and through to the end of lactation produced minimal to slight decreases in femoral bone mineral density and/or cortical circumferences in the offspring at 1.4 to 54 times the expected exposure in humans [see Data].

Data

Animal Data

Reproductive and developmental effects of romosozumab-aqqg were assessed in the rat in a preliminary and definitive embryo-fetal development study, a combined fertility and embryo-development study, and a pre and postnatal development study.

Skeletal malformations including syndactyly and polydactyly occurred in 1 out of 75 litters across all rat reproductive toxicity studies, in the litter of a dam given weekly subcutaneous romosozumab-aqqg doses of 300 mg/kg (equivalent to at least 31 times the clinical exposure observed in humans following a monthly subcutaneous dose of 210 mg, based on area under the concentration-time curve [AUC] comparison).

In the offspring of female rats given weekly romosozumab-aqqg doses from 6 weeks before cohabitation through mating and lactation, femoral periosteal and endocortical circumferences were slightly decreased at 10, 60, and 300 mg/kg (equivalent to 1.4, 18, and 54 times the clinical exposure following a monthly subcutaneous dose of 210 mg, based on AUC comparison). Cortical thickness was increased at 300 mg/kg (equivalent to 54 times expected clinical exposure). Femoral metaphyseal bone mineral density was slightly decreased at 60 and 300 mg/kg (equivalent to 18 and 54 times expected clinical exposure).

8.2 Lactation

Risk Summary

EVENITY is not indicated for use in women of reproductive potential. In animal studies where pregnant rats were given weekly doses of romosozumab-aqqg from 6 weeks before cohabitation through mating and lactation at 10, 60, or 300 mg/kg (equivalent to 1.4, 18 or 54 times the clinical exposure following a monthly subcutaneous dose of 210 mg, based on AUC comparison), romosozumab-aqqg was dose-dependently present in the serum of offspring on postnatal day 21 at 0.01 to 2.4 times maternal exposure due to gestational and/or lactational exposure.

8.4 Pediatric Use

Safety and effectiveness of EVENITY have not been established in pediatric patients.

8.5 Geriatric Use

Of the 6544 postmenopausal women with osteoporosis in the clinical studies of EVENITY, 5234 (80%) were age 65 years and over and 2390 (37%) were age 75 years and over. No overall differences in safety or efficacy were observed between these subjects and younger subjects, and other reported clinical experience has not identified differences in response between the elderly and younger patients, but greater sensitivity of some older individuals cannot be ruled out.

8.7 Renal Impairment

No dose adjustment is required in patients with renal impairment.

Patients with severe renal impairment (estimated glomerular filtration rate [eGFR] 15 to 29 mL/min/1.73 m^2 by MDRD equation) or receiving dialysis are at greater risk of developing hypocalcemia [see Contraindications (4), Warnings and Precautions (5.3) and Adverse Reactions (6.1)]. Monitor calcium concentrations and adequately supplement calcium and vitamin D in patients who have severe renal impairment or are receiving dialysis.

11 DESCRIPTION

Romosozumab-aqqg is a humanized monoclonal antibody (IgG2) produced in a mammalian cell line (Chinese Hamster Ovary) by recombinant DNA technology that binds to and inhibits sclerostin. Romosozumab-aqqg has an approximate molecular weight of 149 kDa.

EVENITY (romosozumab-aqqg) injection is supplied as a sterile, preservative-free, clear to opalescent, colorless to light yellow solution for subcutaneous injection in a single-use prefilled syringe.

Two 105 mg/1.17 mL single-use prefilled syringes are required to administer the recommended 210 mg dose of EVENITY [see Dosage and Administration (2.1)]. Each single-use prefilled syringe delivers 1.17 mL of solution containing 105 mg of romosozumab-aqqg, acetate (3.8 mg), calcium (0.61 mg), polysorbate 20 (0.07 mg) and sucrose (70 mg) in Water for Injection, USP, and sodium hydroxide to a pH of 5.2.

12 CLINICAL PHARMACOLOGY

12.1 Mechanism of Action

EVENITY inhibits the action of sclerostin, a regulatory factor in bone metabolism. EVENITY increases bone formation and, to a lesser extent, decreases bone resorption. Animal studies showed that romosozumab-aqqg stimulates new bone formation on trabecular and cortical bone surfaces by stimulating osteoblastic activity resulting in increases in trabecular and cortical bone mass and improvements in bone structure and strength [see Nonclinical Toxicology (13.2) and Clinical Studies (14.1)].

12.2 Pharmacodynamics

In postmenopausal women with osteoporosis, EVENITY increased the bone formation marker procollagen type 1 N-telopeptide (P1NP) with a peak increase from baseline of approximately 145% compared to placebo 2 weeks after initiating treatment, followed by a return to concentrations seen with placebo at month 9 and a decline from baseline to approximately 15% below the concentration change seen with placebo at month 12.

EVENITY decreased the bone resorption marker type 1 collagen C-telopeptide (CTX) with a maximal reduction from baseline of approximately 55% compared to placebo 2 weeks after initiating treatment. CTX remained below concentrations seen with placebo and was approximately 25% below the concentration change seen with placebo at month 12.

After discontinuation of EVENITY, P1NP levels returned to baseline within 12 months; CTX increased above baseline levels within 3 months and returned toward baseline levels by month 12.

12.3 Pharmacokinetics

Administration of a single dose of 210 mg EVENITY in healthy volunteers resulted in a mean (standard deviation [SD]) maximum romosozumab-aqqg serum concentration (Cmax) of 22.2 (5.8) mcg/mL and a mean (SD) AUC of 389 (127) mcg*day/mL. Steady-state concentrations were achieved by month 3 following the monthly administration of 210 mg to postmenopausal women. The mean trough serum romosozumab-aqqg concentrations at months 3, 6, 9, and 12 ranged from 8 to 13 mcg/mL.

Romosozumab-aqqg exhibited nonlinear pharmacokinetics with exposure increasing greater than dose proportionally (e.g., 550-fold increase in mean AUCinf for the 100-fold increase in subcutaneous doses ranging from 0.1 to 10 mg/kg 0.03 to 3.3 times the approved recommended dosage for a 70 kg woman).

Absorption

The median time to maximum romosozumab-aqqg concentration (Tmax) is 5 days (range: 2 to 7 days).

Distribution

The estimated volume of distribution at steady-state is approximately 3.92 L.

Elimination

Romosozumab-aqqg exhibited nonlinear pharmacokinetics with the clearance of romosozumab-aqqg decreasing as the dose increased. The estimated mean systemic clearance (CL/F) of romosozumab-aqqg was 0.38 mL/hr/kg, following a single subcutaneous administration of 3 mg/kg (the approved recommended dosage for a 70 kg woman). The mean effective t1/2 was 12.8 days after 3 doses of 3 mg/kg (the approved recommended dosage for a 70 kg woman) every 4 weeks.

Metabolism

The metabolic pathway of romosozumab-aqqg has not been characterized. As a humanized IgG2 monoclonal antibody, romosozumab-aqqg is expected to be degraded into small peptides and amino acids via catabolic pathways in a manner similar to endogenous IgG.

Specific Populations

No clinically significant differences in the pharmacokinetics of romosozumab-aqqg were observed based on age (20-89 years), sex, race, disease state (low bone mass or osteoporosis), prior exposure to alendronate, or renal impairment including end-stage renal disease (ESRD) requiring dialysis. The effect of ESRD not requiring dialysis on the pharmacokinetics of romosozumab-aqqg is unknown.

Body Weight

The exposure of romosozumab-aqqg decreases with increasing body weight.

12.6 Immunogenicity

The observed incidence of anti-drug antibodies (ADA) is highly dependent on the sensitivity and specificity of the assay. Differences in assay methods preclude meaningful comparisons of the incidence of ADA in the studies described below with the incidence of ADA in other studies, including those of EVENITY.

In studies of postmenopausal women treated with EVENITY 210 mg monthly for up to 1 year, the immunogenicity of EVENITY was evaluated for up to 2 years using an electrochemiluminescent bridging immunoassay. Among 5914 subjects treated with EVENITY, 18.1% developed antibodies to romosozumab-aqqg. Of the subjects who developed antibodies to romosozumab-aqqg, 4.7% had antibodies that were classified as neutralizing using an in vitro biological assay. Antibodies to romosozumab-aqqg were generally not associated with changes in the efficacy or safety of EVENITY.

Anti-Product Antibody Formation Affecting Pharmacokinetics

Development of anti-romosozumab-aqqg antibodies was associated with reduced serum romosozumab-aqqg concentrations. The presence of anti-romosozumab-aqqg antibodies led to decreased mean romosozumab-aqqg concentrations up to 22%. The presence of neutralizing antibodies led to decreased mean romosozumab-aqqg concentrations up to 63%. These anti-romosozumab-aqqg antibody-associated pharmacokinetic changes were not identified to be clinically significant.

13 NONCLINICAL TOXICOLOGY

13.1 Carcinogenesis, Mutagenesis, Impairment of Fertility

Carcinogenicity

In a rat carcinogenicity study, once-weekly romosozumab-aqqg doses of 3, 10 or 50 mg/kg were administered by subcutaneous injection to Sprague-Dawley rats from 8 weeks up to 98 weeks of age, resulting in systemic exposures that were up to 19 times the systemic exposure observed in humans following a monthly subcutaneous dose of 210 mg EVENITY (based on AUC comparison). Romosozumab-aqqg caused a dose-dependent increase in bone mass with trabecular and cortical bone thickening at all doses. There were no effects of romosozumab-aqqg on mortality and romosozumab-aqqg did not cause significant increases in tumor incidence in male or female rats.

Mutagenicity

Mutagenesis has not been evaluated, as monoclonal antibodies are not expected to alter DNA or chromosomes.

Impairment of Fertility

No effects on fertility were observed in male and female rats given subcutaneous romosozumab-aqqg doses up to 300 mg/kg (up to 54 times the systemic exposure observed in humans following a monthly subcutaneous dose of 210 mg EVENITY, based on AUC comparison). No effects were noted in reproductive organs in rats and cynomolgus monkeys dosed subcutaneously for 6 months with weekly doses up to 100 mg/kg (exposures up to 37 and 90 times, respectively, the systemic exposure observed in humans administered monthly subcutaneous doses of 210 mg based on AUC comparison).

13.2 Animal Toxicology and Pharmacology

No adverse effects were noted in rats and monkeys after 26 once-weekly subcutaneous romosozumab-aqqg doses up to 100 mg/kg, equivalent to systemic exposures of 37 and 90 times, respectively, the systemic exposure observed in humans following a monthly subcutaneous dose of 210 mg EVENITY (based on AUC comparison).

Bone safety studies of up to 12-month duration were conducted in ovariectomized rats and monkeys with once-weekly romosozumab-aqqg doses yielding exposures ranging from 1 to 21 times the systemic exposure in humans given monthly doses of 210 mg, based on AUC comparison. Romosozumab-aqqg increased bone mass and improved cancellous bone microarchitecture and cortical bone geometry by increasing bone formation on periosteal, endocortical, and trabecular surfaces, and decreasing bone resorption on trabecular and endocortical surfaces. The increases in bone mass were significantly correlated with increases in bone strength. In rats and monkeys, bone quality was maintained at all skeletal sites at doses ranging from 1 to 21 times human exposure, and slightly improved in vertebrae at 19 to 21 times human exposure. There was no evidence of mineralization defects, osteoid accumulation, or woven bone formation.

14 CLINICAL STUDIES

14.1 Treatment of Osteoporosis in Postmenopausal Women

Study 1 (NCT01575834) was a randomized, double-blind, placebo-controlled study of postmenopausal women aged 55 to 90 years (mean age of 71 years) with bone mineral density (BMD) T-score less than or equal to −2.5 at the total hip or femoral neck. Women were randomized to receive subcutaneous injections of either EVENITY (N = 3589) or placebo (N = 3591) for 12 months. At baseline, 18% of women had a vertebral fracture. After the 12-month treatment period, women in both arms transitioned to open-label anti-resorptive therapy (denosumab) for 12 months while remaining blinded to their initial treatment. Women received 500 to 1000 mg calcium and 600 to 800 international units vitamin D supplementation daily. The coprimary efficacy endpoints were new vertebral fracture at month 12 and month 24.

Effect on Fractures

EVENITY significantly reduced the incidence of new vertebral fractures through month 12 compared to placebo. In addition, the significant reduction in fracture risk persisted through the second year in women who received EVENITY during the first year and transitioned to denosumab compared to those who transitioned from placebo to denosumab (see Table 2).

Table 2. Effect of EVENITY on the Incidence and Risk of Fractures in Study 1
 | Proportion of Women with Fractures |  | Absolute Risk Reduction (%) (95% CI) [Absolute and relative risk reduction are based on the Mantel-Haenszel method adjusting for age and prevalent vertebral fracture strata.] | Relative Risk Reduction (%) (95% CI) | p-value [P-value is based on logistic regression model adjusting for age and prevalent vertebral fracture strata.]
At Month 12 | Placebo (N = 3591) | EVENITY (N = 3589)
New vertebral fracture | 1.8% | 0.5% | 1.3 (0.8, 1.8) | 73 (53, 84) | < 0.001
At Month 24 | Placebo Followed by Denosumab (N = 3591) | EVENITY Followed by Denosumab (N = 3589)
New vertebral fracture | 2.5% | 0.6% | 1.9 (1.3, 2.5) | 75 (60, 84) | < 0.001
N = Number of subjects randomized

EVENITY significantly reduced the incidence of clinical fracture (a composite endpoint of symptomatic vertebral fracture and nonvertebral fracture) at 12 months. However, 88% of these clinical fractures were nonvertebral fractures and the incidence of nonvertebral fractures was not statistically significantly different when comparing EVENITY-treated women to placebo-treated women at month 12 or month 24.

Effect on Bone Mineral Density (BMD)

EVENITY significantly increased BMD at the lumbar spine, total hip, and femoral neck compared with placebo at month 12. The treatment differences in BMD were 12.7% at the lumbar spine, 5.8% at the total hip, and 5.2% at the femoral neck.

Following the transition from EVENITY to denosumab at month 12, BMD continued to increase through month 24. In patients who transitioned from placebo to denosumab, BMD also increased with denosumab use. The differences in BMD achieved at month 12 between EVENITY and placebo patients were overall maintained at month 24, when comparing patients who transitioned from EVENITY to denosumab to those who transitioned from placebo to denosumab. There was no evidence of differences in effects on BMD at the lumbar spine or total hip across subgroups defined by baseline age, baseline BMD, or geographic region.

After EVENITY discontinuation, BMD returns to approximately baseline levels within 12 months in the absence of follow-on anti-resorptive therapy [see Indications and Usage (1.2)].

Bone Histology and Histomorphometry

A total of 154 transiliac crest bone biopsy specimens were obtained from 139 postmenopausal women with osteoporosis at month 2, month 12, and/or month 24. All of these biopsies were adequate for qualitative histology and 138 (90%) were adequate for full quantitative histomorphometry assessment. Qualitative histology assessments from women treated with EVENITY showed normal bone architecture and quality at all time points. There was no evidence of woven bone, mineralization defects, or marrow fibrosis.

Histomorphometry assessments on biopsies at months 2 and 12 compared the effect of EVENITY with placebo (15 specimens at month 2 and 39 specimens at month 12 in the EVENITY group, 14 specimens at month 2 and 31 specimens at month 12 in the placebo group). At month 2 in women treated with EVENITY, histomorphometric indices of bone formation at trabecular and endocortical surfaces were increased. These effects on bone formation were accompanied by a decrease in indices of bone resorption. At month 12, both bone formation and resorption indices were decreased with EVENITY, while bone volume, and trabecular and cortical thickness were increased.

Study 2 (NCT01631214) was a randomized, double-blind, alendronate-controlled study of postmenopausal women aged 55 to 90 years (mean age of 74 years) with BMD T-score less than or equal to −2.5 at the total hip or femoral neck and either one moderate or severe vertebral fracture or two mild vertebral fractures, or BMD T-score less than or equal to -2.0 at the total hip or femoral neck and either two moderate or severe vertebral fractures or a history of a proximal femur fracture. Women were randomized (1:1) to receive either monthly subcutaneous injections of EVENITY (N = 2046) or oral alendronate 70 mg weekly (N = 2047) for 12 months, with 500 to 1000mg calcium and 600 to 800 international units vitamin D supplementation daily. After the 12-month treatment period, women in both arms transitioned to open-label alendronate 70 mg weekly while remaining blinded to their initial treatment.

This was an event-driven trial. The two primary efficacy endpoints were the incidence of morphometric vertebral fracture at 24 months and time to the first clinical fracture through the primary analysis period, which ended when at least 330 subjects had a clinical fracture and all subjects had completed the 24-month visit. Clinical fracture was a composite endpoint of nonvertebral fracture and symptomatic vertebral fracture.

Effect on Fractures

EVENITY significantly reduced the incidence of new vertebral fracture at 24 months (see Table 3).

Table 3. Effect of EVENITY on the Incidence of New Vertebral Fractures in Study 2
 | Proportion of Women with Fracture (%) |  | Risk Reduction |  | p-value [P-value is based on logistic regression model for new vertebral fracture) adjusting for age strata, baseline total hip BMD T-score, and presence of severe vertebral fracture at baseline.]
 | Alendronate Alone (N = 2047) | EVENITY Followed by Alendronate (N = 2046) | Absolute Risk Reduction (%) (95% CI) [Absolute and relative risk reductions are based on the Mantel-Haenszel method adjusting for age strata, baseline total hip BMD T-score (≤ -2.5, > -2.5), and presence of severe vertebral fracture at baseline.] | Relative Risk Reduction (%) (95% CI)
New vertebral fracture through Month 24 | 8.0% | 4.1% | 4.0 (2.5, 5.6) | 50 (34, 62) | < 0.001
N = Number of subjects randomized

EVENITY significantly reduced the risk of clinical fracture through the end of the primary analysis period (see Table 4). This was an event-driven trial and the duration of follow-up varied across subjects. The median duration of subject follow-up for the primary analysis period was 33 months. Subjects with nonvertebral fracture comprised 83% of the subjects with clinical fracture during the primary analysis period.

Table 4. Effect of EVENITY on the Risk of Clinical Fractures in Study 2
 | Proportion of Women with Fracture (%) [% = number of subjects who had a clinical fracture through the primary analysis period/N*100%; the duration of follow-up varied across subjects.] |  | Hazard Ratio (95% CI) [Hazard ratio and P-value are based on Cox proportional hazards model adjusting for age strata, baseline total hip BMD T-score, and presence of severe vertebral fracture at baseline.] | p-value
 | Alendronate Alone (N = 2047) | EVENITY Followed by Alendronate (N = 2046) | Hazard Ratio (95% CI) [Hazard ratio and P-value are based on Cox proportional hazards model adjusting for age strata, baseline total hip BMD T-score, and presence of severe vertebral fracture at baseline.] | p-value
Clinical fracture through primary analysis period [Primary analysis period ended when clinical fracture events were confirmed for at least 330 subjects and all subjects completed the month 24 study visit. The median duration of follow-up for the primary analysis period was 33 months.] | 13.0% | 9.7% | 0.73 (0.61, 0.88) | < 0.001
N = Number of subjects randomized

EVENITY followed by alendronate also significantly reduced the risk of nonvertebral fracture through the primary analysis period (with a median follow-up of 33 months), with a hazard ratio of 0.81 (95% CI: 0.66, 0.99; p = 0.04) compared to alendronate alone.

Effect on Bone Mineral Density (BMD)

EVENITY significantly increased BMD at the lumbar spine, total hip, and femoral neck compared with alendronate at month 12. The treatment differences in BMD were 8.7% at the lumbar spine, 3.3% at the total hip, and 3.2% at the femoral neck.

Twelve months of treatment with EVENITY followed by 12 months of treatment with alendronate significantly increased BMD compared with alendronate alone. The BMD increase with EVENITY over alendronate observed at month 12 was maintained at month 24. The treatment differences in BMD at month 24 were 8.1% at the lumbar spine, 3.8% at the total hip, and 3.8% at the femoral neck.

There was no evidence of differences in effects on BMD at the lumbar spine or total hip across subgroups defined by baseline age, baseline BMD, or geographic region.

16 HOW SUPPLIED/STORAGE AND HANDLING

16.1 How Supplied

EVENITY (romosozumab-aqqg) injection is a clear to opalescent, colorless to light yellow solution for subcutaneous injection supplied in a single-use prefilled syringe.

Each single-use prefilled syringe contains 105 mg of EVENITY in a deliverable volume of 1.17 mL. To deliver a full dose, inject two 105 mg/1.17 mL EVENITY prefilled syringes, one after the other for a total dose of 210 mg.

- NDC 55513-509-02: Carton of two 105 mg/1.17 mL single-use glass prefilled syringes with automatic needle guard.
- NDC 55513-998-02: Carton of two 105 mg/1.17 mL single-use glass prefilled syringes.
- NDC 55513-880-02: Carton of two 105 mg/1.17 mL single-use plastic prefilled syringes.

The single-use prefilled syringe is not made with natural rubber latex.

16.2 Storage and Handling

- Refrigerate EVENITY at 2°C to 8°C (36°F to 46°F) in the original carton to protect from light. Do not freeze. Do not shake.
- If removed from the refrigerator, EVENITY can be kept at room temperature up to 25°C (77°F) in the original carton and must be used within 30 days. If not used within 30 days, discard EVENITY.
- Do not expose EVENITY to temperatures above 25°C (77°F).

17 PATIENT COUNSELING INFORMATION

Advise the patient to read the FDA-approved patient labeling (Medication Guide).

Major Adverse Cardiac Events

Advise patients to seek immediate medical attention if they experience signs or symptoms of a myocardial infarction or stroke [see Boxed Warning, Warnings and Precautions (5.1) and Adverse Reactions (6.1)].

Hypersensitivity Reactions

Advise patients to seek immediate medical attention if they experience signs or symptoms of a hypersensitivity reaction including angioedema, erythema multiforme, dermatitis, rash, and urticaria [see Warnings and Precautions (5.2) and Adverse Reactions (6.1)].

Calcium and Vitamin D Supplements to Prevent Hypocalcemia

Advise patients to take calcium and vitamin D supplements daily to reduce the risk of hypocalcemia. Advise patients to seek immediate medical attention for symptoms of hypocalcemia [see Dosage and Administration (2.1), Warnings and Precautions (5.3) and Adverse Reactions (6.1)].

Osteonecrosis of the Jaw

Advise patients to practice good oral hygiene during treatment with EVENITY and tell their dentist that they are receiving EVENITY before having dental work. [see Warnings and Precautions (5.4) and Adverse Reactions (6.1)].

Atypical Femoral Fracture

Advise patients to report signs and symptoms that could be consistent with impending atypical femoral fracture including new or unusual thigh, hip, or groin pain [see Warnings and Precautions (5.5) and Adverse Reactions (6.1)].

EVENITY® (romosozumab-aqqg)

Manufactured by:
Amgen Inc.
One Amgen Center Drive
Thousand Oaks, California 91320-1799
U.S. License No. 1080

Patent: http://pat.amgen.com/EVENITY/

© 2019, 2020, 2024, 2026 Amgen Inc. All rights reserved.

1xxxxxx- v6

MEDICATION GUIDE
EVENITY® (E-ven-i-tee)
(romosozumab-aqqg)
Injection, for subcutaneous use

What is the most important information I should know about EVENITY?
EVENITY can cause serious side effects, including:

- increased risk of having a heart attack, stroke, or death from a cardiovascular (heart or blood vessel) problem. Call your healthcare provider or get emergency help right away if you have any of the symptoms listed below.
  - Symptoms of heart attack may include:
    - chest pain or pressure
    - shortness of breath
    - feeling light-headed or dizzy
  - Symptoms of stroke may include:
    - headache
    - numbness or weakness in face, arm, or legs
    - difficulty talking
    - changes in vision or loss of balance

Before you receive EVENITY, tell your healthcare provider if you have had a heart attack or stroke, especially if it has happened in the past year.
See “What are the possible side effects of EVENITY?” below for other side effects of EVENITY.

What is EVENITY?
EVENITY is a prescription medicine used to:

- treat osteoporosis (thinning and weakening of bone) in women after menopause (“change of life”) who:
  - are at high risk of fracture (broken bone), or
  - cannot use another osteoporosis medicine or other osteoporosis medicines did not work well.

It is not known if EVENITY is safe and effective in children.

Do not receive EVENITY if you:

- have been told by your healthcare provider that your blood calcium level is too low.
- are allergic to romosozumab or any of the ingredients in EVENITY. See the end of this Medication Guide for a complete list of ingredients in EVENITY.

Before receiving EVENITY, tell your healthcare provider about all your medical conditions, including if you:

- have a history of other heart or blood vessel problems
- have low blood calcium
- cannot take daily calcium and vitamin D
- have kidney problems or are on kidney dialysis
- plan to have dental surgery or teeth removed

Tell your healthcare provider about all the medicines you take, including prescription and over-the-counter medicines, vitamins, and herbal supplements.

How will I receive EVENITY?

- EVENITY is an injection that will be given to you by your healthcare provider. EVENITY is injected under your skin (subcutaneous).
- You will receive an EVENITY dose (2 injections) 1 time every month for 12 doses.
- You should take calcium and vitamin D while you receive EVENITY.
- If you miss a dose of EVENITY, contact your healthcare provider as soon as possible to schedule your next dose. Your next dose of EVENITY should then be scheduled every month from the date of the last injection.
- You should take good care of your teeth and gums while you receive EVENITY. You should tell your dentist that you are receiving EVENITY before you have dental work.

What are the possible side effects of EVENITY?
EVENITY may cause serious side effects, including:
See “What is the most important information I should know about EVENITY?”

- Serious allergic reactions. Serious allergic reactions have happened in people who receive EVENITY. Call your healthcare provider or go to the nearest emergency room right away if you have any symptoms of a serious allergic reaction. Symptoms of a serious allergic reaction may include:
  ○ rash
  ○ hives
  ○ swelling of the face, lips, mouth, tongue, or throat which may cause difficulty in swallowing or breathing
- Low calcium levels in your blood (hypocalcemia). EVENITY may lower the calcium levels in your blood. Your low blood calcium should be treated before you receive EVENITY. Call your healthcare provider if you have symptoms of low blood calcium such as:
  ○ spasms, twitches, or cramps in your muscles
  ○ numbness or tingling in your fingers, toes or around your mouth
- Severe jaw bone problems (osteonecrosis). Severe jaw bone problems may happen when you take EVENITY. Your healthcare provider should examine your mouth before you start EVENITY.
  ○ Your healthcare provider may tell you to see your dentist before you start EVENITY. Ask your healthcare provider or dentist about good mouth care.
- Unusual thigh bone fractures. Symptoms of this type of fracture include:
  ○ new or unusual pain in your hip, groin, or thigh.

The most common side effects of EVENITY include:

• joint pain
• headache

These are not all the possible side effects of EVENITY.
Call your healthcare provider for medical advice about side effects. You may report side effects to FDA at 1-800-FDA-1088.

How should I store EVENITY if I need to pick it up from a pharmacy?

- Keep EVENITY in a refrigerator at 36°F to 46°F (2°C to 8°C) in the original carton to protect it from light.
- Do not freeze EVENITY.
- Do not shake EVENITY.
- When you remove EVENITY from the refrigerator, EVENITY must be kept at room temperature up to 77°F (25°C) in the original carton and must be used within 30 days. EVENITY should be thrown away if taken out of the refrigerator and not used within 30 days.
- Do not keep EVENITY at temperatures above 77°F (25°C). Warm temperatures will affect how EVENITY works.

Keep EVENITY and all medicines out of the reach of children.

General information about EVENITY
Medicines are sometimes prescribed for purposes other than those listed in a Medication Guide. You can ask your pharmacist or healthcare provider for information about EVENITY that is written for health professionals.

What are the ingredients in EVENITY?
Active ingredient: romosozumab-aqqg
Inactive ingredients: acetate, calcium, polysorbate 20, sodium hydroxide, sucrose and water for injection.

Manufactured by: Amgen Inc., One Amgen Center Drive, Thousand Oaks, CA 91320-1799
US License No. 1080 © 2019, 2020, 2024 Amgen Inc. All rights reserved. 1xxxxxx – v3
For more information, go to www.evenity.com or call Amgen at 1-800-772-6436.

This Medication Guide has been approved by the U.S. Food and Drug Administration.

Revised: 10/2024

PACKAGE LABEL

PRINCIPAL DISPLAY PANEL

2 x 105 mg/1.17 mL Single-Use Prefilled Syringe

NDC 55513-880-02

EVENITY®

(romosozumab-aqqg)

injection

For Healthcare

Provider Use Only

105 mg/1.17 mL + 105 mg/1.17 mL = 1 Dose

210 mg/2.34 mL

2 x 105 mg/1.17 mL

105 mg/1.17 mL

For Subcutaneous Use Only

Sterile Solution – No Preservative

Store Refrigerated at 2°C to 8°C (36°F to 46°F). Do not Freeze or Shake.

Store in carton to protect from light.

Keep out of the sight and reach of children.

ATTENTION: Provide the enclosed Medication

Guide to each patient. For more copies

see EVENITY.com or call 1-800-77AMGEN.

2 syringes must be administered for

a full 210 mg/2.34 mL dose

Rx Only

AMGEN® ucb

PRINCIPAL DISPLAY PANEL - 105 mg/1.17 mL Syringe Carton

2 x 105 mg/1.17 mL Single-Use Prefilled Syringe

NDC 55513-998-02

EVENITY®
(romosozumab-aqqg)
injection

For Healthcare
Provider Use Only

105 mg/
1.17 mL
+
105 mg/
1.17 mL
= 1 Dose

210 mg/
2.34 mL

2 x 105 mg/1.17 mL

105 mg/1.17 mL
For Subcutaneous Use Only

Sterile Solution – No Preservative

Store Refrigerated at 2°C to 8°C (36°F to 46°F). Do not Freeze or Shake.
Store in carton to protect from light.

Keep out of the sight and reach of children.

ATTENTION: Provide the enclosed Medication
Guide to each patient. For more copies

see EVENITY.com or call 1-800-77AMGEN.

2 syringes must be administered for
a full 210 mg/2.34 mL dose

Rx Only

AMGEN ucb

PRINCIPAL DISPLAY PANEL - 105 mg/1.17 mL Syringe Carton

2 x 105 mg/1.17 mL Single-Use Prefilled Syringe

NDC 55513-509-02

EVENITY®
(romosozumab-aqqg)
injection

For Healthcare Provider Use Only

105 mg/
1.17 mL
+
105 mg/
1.17 mL
= 1 Dose

210 mg/
2.34 mL

105 mg/1.17 mL
For Subcutaneous Use Only

Sterile Solution – No Preservative

Dispense in this sealed carton

ATTENTION: Provide the enclosed Medication
Guide to each patient. For more copies
see EVENITY.com or call 1-800-77AMGEN.

2 syringes must be administered for
a full 210 mg/2.34 mL dose

Rx Only

AMGEN ucb